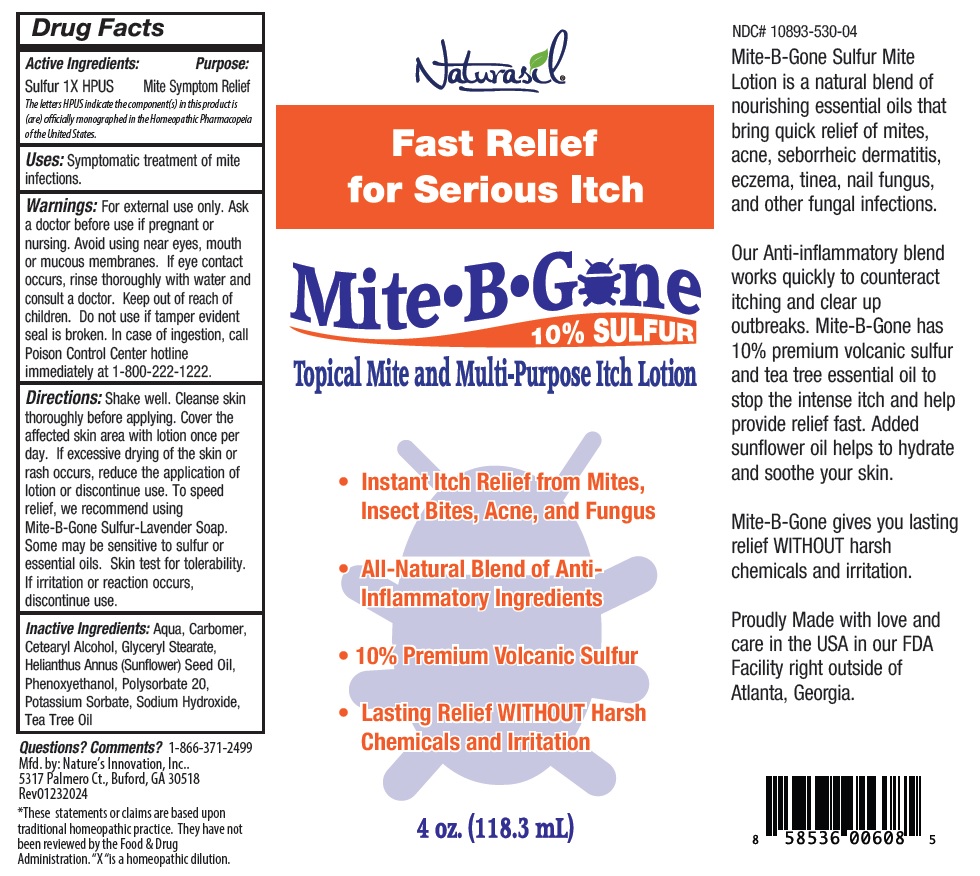 DRUG LABEL: Naturasil Mite B Gone
NDC: 10893-530 | Form: LOTION
Manufacturer: Nature's Innovation, Inc.
Category: homeopathic | Type: HUMAN OTC DRUG LABEL
Date: 20240118

ACTIVE INGREDIENTS: SULFUR 1 [hp_X]/118.3 mL
INACTIVE INGREDIENTS: WATER; CARBOMER HOMOPOLYMER, UNSPECIFIED TYPE; CETOSTEARYL ALCOHOL; GLYCERYL MONOSTEARATE; SUNFLOWER OIL; PHENOXYETHANOL; POLYSORBATE 20; POTASSIUM SORBATE; SODIUM HYDROXIDE; TEA TREE OIL

Naturasil Mite B Gone Topical Mite and Multi-Purpose Itch Lotion

Active Ingredients:

Sulfur 1X HPUS

The letters HPUS indicate the component(s) in this product is (are) officially monographed in the Homeopathic Pharmacopeia of the United States.

Purpose:

Mite Symptom Relief

INDICATIONS AND USAGE

Uses: Symptomatic treatment of mite infections.

WARNINGS

Warnings: For external use only. Ask a doctor before use if pregnant or nursing. Avoid using near eyes, mouth or mucous membranes. If eye contact occurs, rinse thoroughly with water and consult a doctor.

Keep out of reach of children. Do not use if tamper evident seal is broken. In case of ingestion, call Poison Control Center hotline immediately at 1-800-222-1222.

DOSAGE AND ADMINISTRATION

Directions: Shake well. Cleanse skin thoroughly before applying. Cover the affected skin area with lotion once per day. If excessive drying of the skin or rash occurs, reduce the application of lotion or discontinue use. To speed relief, we recommend using Mite-B-Gone Sulfur-Lavender Soap. Some may be sensitive to sulfur or essential oils. Skin test for tolerability. If irritation or reaction occurs, discontinue use.

INACTIVE INGREDIENT

Inactive Ingredients: Aqua, Carbomer, Cetearyl Alcohol, Glyceryl Stearate, Helianthus Annus (Sunflower) Seed Oil, Phenoxyethanol, Polysorbate 20, Potassium Sorbate, Sodium Hydroxide, Tea Tree Oil

Fast Relief for Serious Itch

10% SULFUR

• Instant Itch Relief from Mites, Insect Bites, Acne, and Fungus

• All-Natural Blend of Anti-Inflammatory Ingredients

• 10% Premium Volcanic Sulfur

• Lasting Relief WITHOUT Harsh Chemicals and Irritation

Mite-B-Gone Sulfur Mite Lotion is a natural blend of nourishing essential oils that bring quick relief of mites, acne, seborrheic dermatitis, eczema, tinea, nail fungus, and other fungal infections.

Our Anti-inflammatory blend works quickly to counteract itching and clear up outbreaks. Mite-B-Gone has 10% premium volcanic sulfur and tea tree essential oil to stop the intense itch and help provide relief fast. Added sunflower oil helps to hydrate and soothe your skin.

Mite-B-Gone gives you lasting relief WITHOUT harsh chemicals and irritation.

Proudly Made with love and care in the USA in our FDA Facility right outside of Atlanta, Georgia.

Questions? Comments? 1-866-371-2499
Mfd. by: Nature’s Innovation, Inc.
5317 Palmero Ct., Buford, GA 30518
Rev01182024

*These statements or claims are based upon traditional homeopathic practice. They have not been reviewed by the Food & Drug Administration. "X" is a homeopathic dilution.